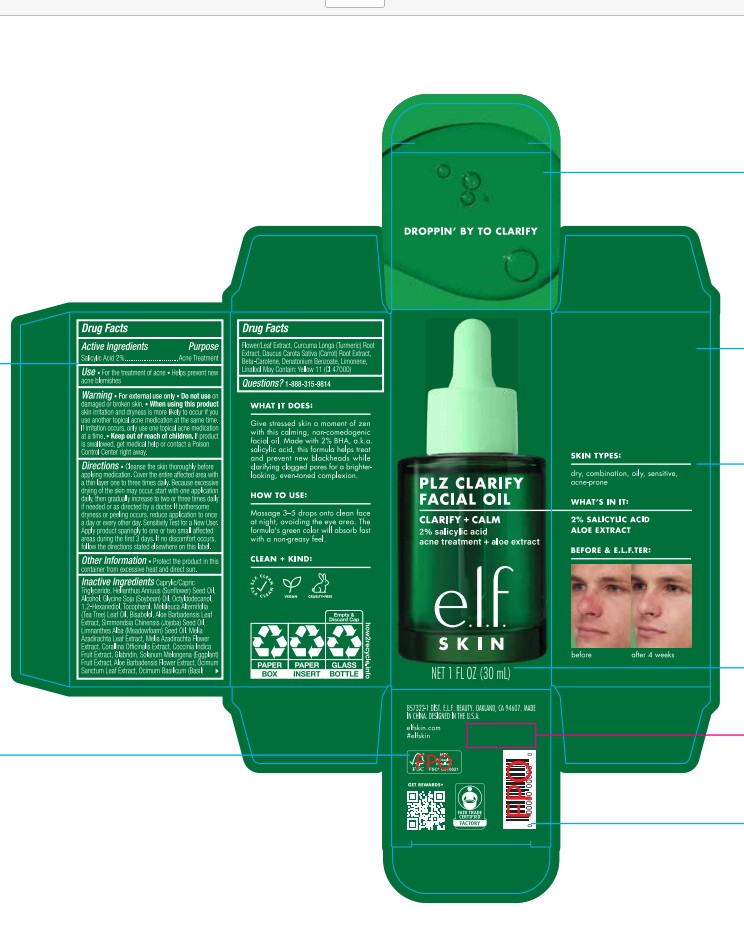 DRUG LABEL: e.l.f. PLZ Clarify Facial Oil
NDC: 76354-419 | Form: LIQUID
Manufacturer: e.l.f. Cosmetics, Inc.
Category: otc | Type: HUMAN OTC DRUG LABEL
Date: 20251214

ACTIVE INGREDIENTS: SALICYLIC ACID 20 mg/1 mL
INACTIVE INGREDIENTS: YELLOW 11; LIMONENE, (+)-; GLABRIDIN; BETA-CAROTENE; MELALEUCA ALTERNIFOLIA (TEA TREE) LEAF OIL; OCIMUM BASILICUM FLOWERING TOP; OCTYLDODECANOL; CORALLINA OFFICINALIS; DAUCUS CAROTA SATIVA (CARROT) SEED OIL; LINALOOL; ALOE BARBADENSIS LEAF; COCCINIA GRANDIS FRUIT; SOLANUM MELONGENA ROOT; 1,2-HEXANEDIOL; BISABOLOL; ALOE VERA FLOWER; CURCUMA LONGA (TURMERIC) ROOT; HELIANTHUS ANNUUS (SUNFLOWER) SEED OIL; SOYBEAN OIL; TOCOPHEROL; LIMNANTHES ALBA (MEADOWFOAM) SEED OIL; ALCOHOL; CAPRYLIC/CAPRIC TRIGLYCERIDE; MELIA AZADIRACHTA LEAF; SIMMONDSIA CHINENSIS (JOJOBA) SEED OIL; DENATONIUM BENZOATE

e.l.f. PLZ Clarify Facial Oil

Active Ingredients

Salicylic Acid 2%

Purpose

Acne Treatment

Uses

For the treatment of acne.
Helps prevent new acne from forming.

Warning

For external use only.

Do not use

on damaged or broken skin.

When using this product

skin irritation and dryness is more likely to occur if you use another topical acne medication at the same time. If irritation occurs, only use one topical acne medication at a time.

Keep out of reach of children.

If product is swallowed, get medical help or contact Poison Control Center right away.

Directions

Cleanse the skin thoroughly before applying medication. Cover the entire affected area with a thin layer one to three times daily. Because excessive drying of the skin may occur, start with one application daily, then gradually increase to two or three times daily if needed or as directed by a doctor. If bothersome dryness or peeling occurs, reduce application to once a day or every other day. Sensitivity Test for a New User. Apply product sparingly to one or two small affected areas during the first 3 days. If no discomfort occurs, follow the directions stated elsewhere on this label.

Inactive Ingredients:

Caprylic/Capric Triglyceride, Helianthus Annuus (Sunflower) Seed Oil, Alcohol, Glycine Soja (Soybean) Oil, Octyldodecanol, 1,2-Hexanediol, Tocopherol, Melaleuca Alternifolia (Tea Tree) Leaf Oil, Bisabolol, Aloe Barbadensis Leaf Extract, Simmondsia Chinensis (Jojoba) Seed Oil, Limnanthes Alba (Meadowfoam) Seed Oil, Melia Azadirachta Leaf Extract, Melia Azadirachta Flower Extract, Corallina Officinalis Extract, Coccinia Indica Fruit Extract, Glabridin, Solanum Melongena (Eggplant) Fruit Extract, Aloe Barbadensis Flower Extract, Ocimum Sanctum Leaf Extract, Ocimum Basilicum (Basil) Flower/Leaf Extract, Curcuma Longa (Turmeric) Root Extract, Daucus Carota Sativa (Carrot) Root Extract, Beta-Carotene, Denatonium Benzoate, Limonene, Linalool May Contain: Yellow 11 (CI 47000)

Questions?

1-888-315-9814